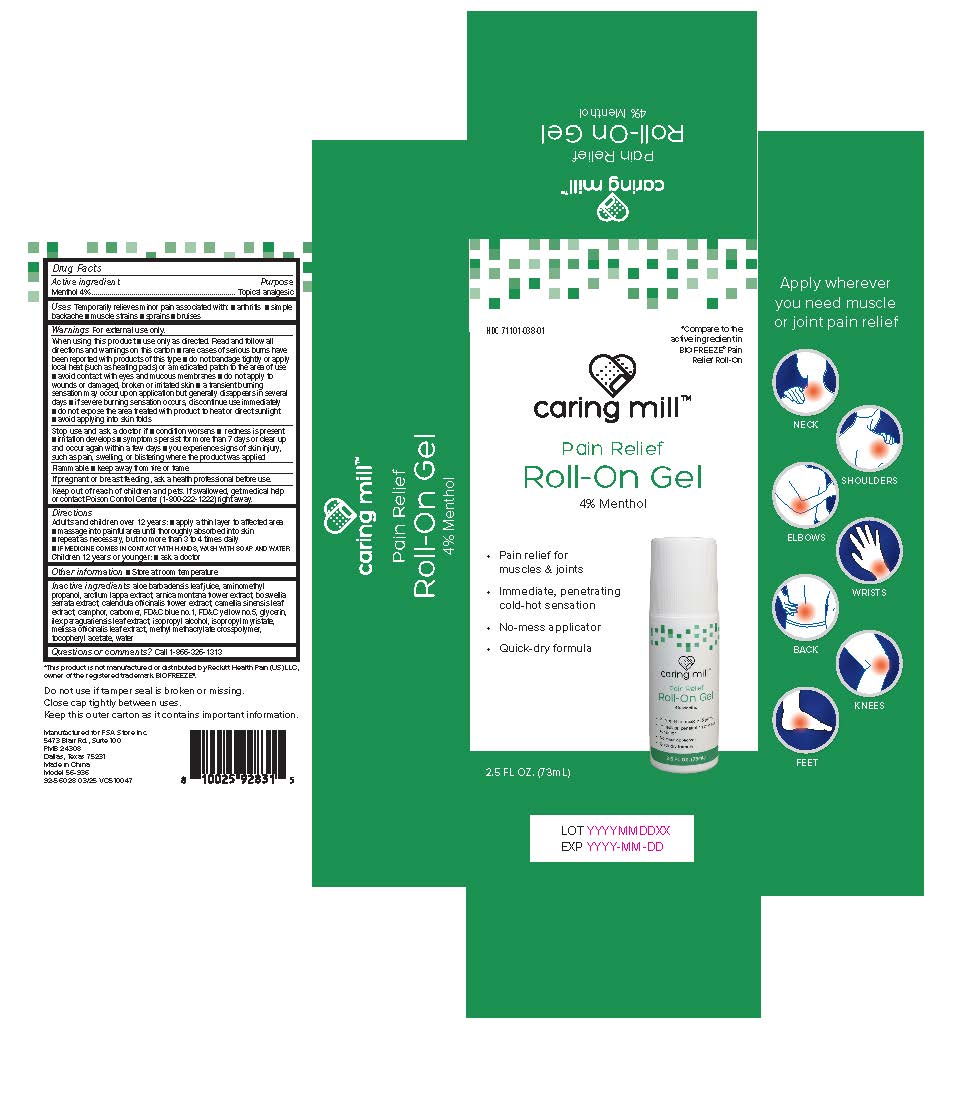 DRUG LABEL: Caring Mills Menthol 4% Roll-On
NDC: 71101-038 | Form: GEL
Manufacturer: Veridian Healthcare
Category: otc | Type: HUMAN OTC DRUG LABEL
Date: 20250929

ACTIVE INGREDIENTS: MENTHOL 4 g/1 mL
INACTIVE INGREDIENTS: GLYCERIN; ALOE VERA LEAF; CARBOMER 940; CAMPHOR (NATURAL); AMINOMETHYL PROPANOL; ALCOHOL; ARNICA MONTANA FLOWER; WATER; ISOPROPYL MYRISTATE; CALENDULA OFFICINALIS FLOWER; .ALPHA.-TOCOPHEROL ACETATE; MELISSA OFFICINALIS LEAF; ARCTIUM LAPPA WHOLE; GREEN TEA LEAF; ILEX PARAGUARIENSIS LEAF; INDIAN FRANKINCENSE; METHYL METHACRYLATE/GLYCOL DIMETHACRYLATE CROSSPOLYMER; FD&C YELLOW NO. 5; FD&C BLUE NO. 1

Caring Mills Menthol 4% Roll-On

Caring Mills Menthol 4% Roll-On

Active ingredient

Menthol 4%

Purpose

Topical analgesic

Uses

Uses Temporarily relieves minor pain associated with: ■ arthritis ■ simple backache ■ muscle strains ■ sprains ■ bruises

Warnings

For external use only

When using this product

■ use only as directed. Read and follow all directions and warnings on this carton

■ rare cases of serious burns have been reported with products of this type

■ do not bandage tightly or apply local heat (such as heating pads) or a medicated patch to the area of use
■ avoid contact with eyes and mucous membranes

■ do not apply to wounds or damaged, broken or irritated skin

■ a transient burning sensation may occur upon application but generally disappears in several days

■ if severe burning sensation occurs, discontinue use immediately
■ do not expose the area treated with the product to heat or direct sunlight
■ avoid applying into skin folds

Stop use and ask a doctor if

- condition worsens
- redness is present
- irritation develops
- symptoms persist for more than 7 days or clear up and occur again within a few days
- you experience signs of skin injury, such as pain, swelling, or blistering where the product was applied

Flammable■ Keep away from fire or flame

If pregnant or breast-feeding,

ask a health professional before use.

Keep out of reach of children.

If swallowed, get medical help or contact a Poison Control Center (1-800-222-1222) right away.

Directions

Adults and children over 12 years:■ apply a thin layer to affected area
■ massage into painful area until thoroughly absorbed into skin
■ repeat as necessary, but no more than 3 to 4 times daily
■ IF MEDICINE COMES IN CONTACT WITH HANDS, WASH WITH SOAP AND WATER
Children 12 years or younger:■ ask a doctor

Inactive ingredients

aloe barbadensis leaf juice, aminomethyl propanol, arctium lappa extract, arnica montana flower extract, boswellia serrata extract, calendula officinalis flower extract, camellia sinensis leaf extract, camphor, carbomer, FD&C blue no.1, FD&C yellow no.5, glycerin, ilex paraguariensis leaf extract, isopropyl alcohol, isopropyl myristate, melissa officinalis leaf extract, methyl methacrylate crosspolymer, tocopheryl acetate, water

Questions or comments

Call 1-866-326-1313